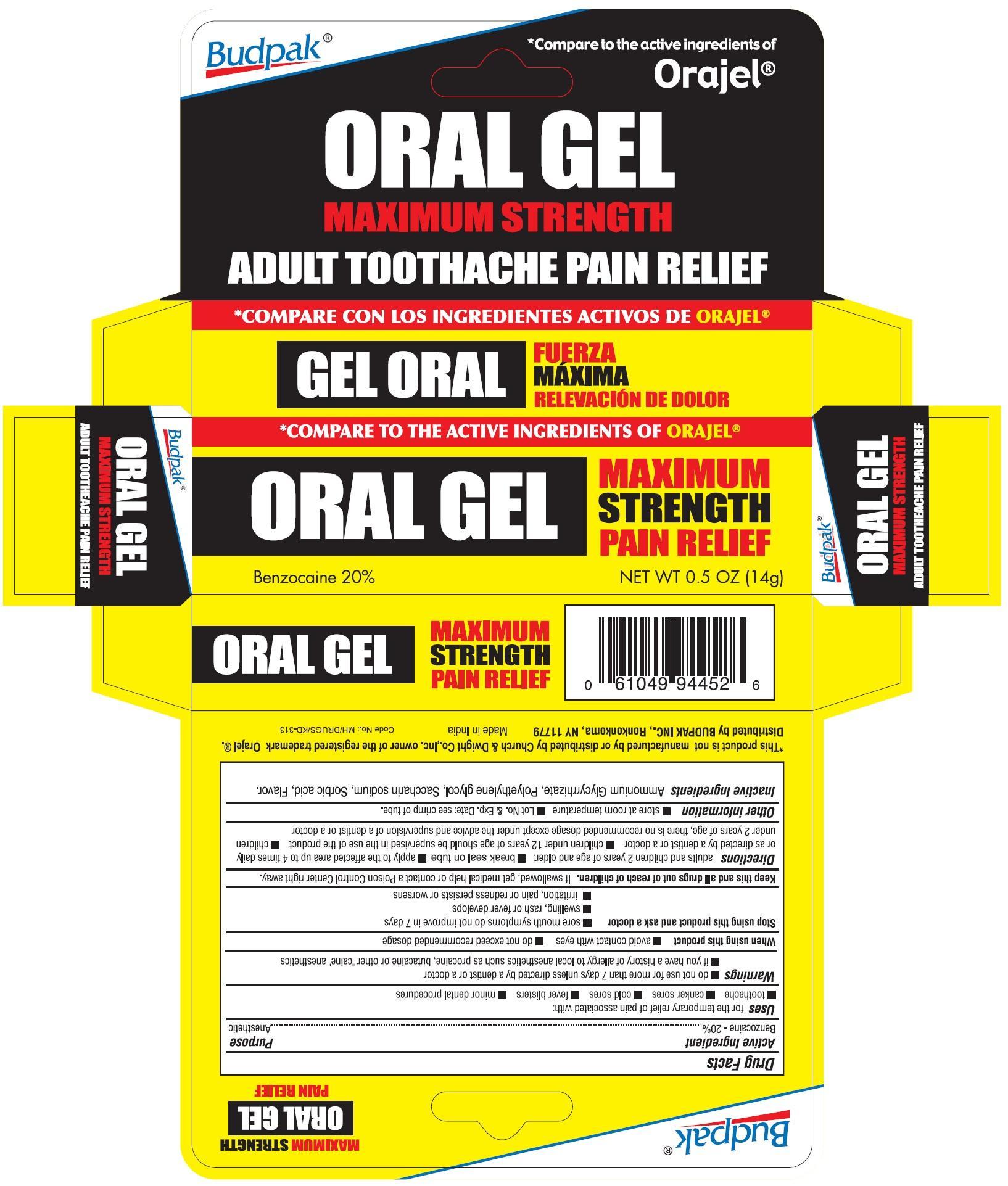 DRUG LABEL: Budpak Oral Maximum Strength
NDC: 27293-019 | Form: GEL
Manufacturer: Budpak Inc.
Category: otc | Type: HUMAN OTC DRUG LABEL
Date: 20130608

ACTIVE INGREDIENTS: BENZOCAINE 0.2 g/1 g
INACTIVE INGREDIENTS: GLYCYRRHIZIN, AMMONIATED; POLYETHYLENE GLYCOLS; SACCHARIN SODIUM; SORBIC ACID

Active Ingredient

Benzocaine 20%

Purpose

Anesthetic

Uses

for the temporary relief of pain associated with:

- toothache
- canker sores
- cold sores
- fever blisters
- minor dental procedures

Warnings

- do not use for more than 7 days unless directed by a dentist or a doctor
- if you have a history of allergy to local anesthetics such as procaine, butacaine or other "caine" anesthetics

When using this product

- avoid contact with the eyes
- do not exceed recommended dosage

Stop using this product and ask a doctor

- sore mouth symptoms do not improve in 7 days
- swelling, rash or fever develops
- irritation, pain or redness persists or worsens

KEEP OUT OF REACH OF CHILDREN

Keep this and all drugs out of reach of children.

If swallowed, get medical help or contact a Poison Control Center right away.

Directions

adults and children 2 years of age and older:

- break seal on tube
- apply to the affected area up to 4 times daily or as directed by a dentist or a doctor
- children under 12 years of age should be supervised in the use of the product
- children under 2 years of age, there is no recommended dosage except under the advice and supervision of a dentist or a doctor

Other Information

- store at room temperature.
- Lot. No and Exp. Date: see crimp of tube.

Inactive Ingredients

Ammonium Glycyrrhizate, Polyethylene glycol, Saccharin sodium, Sorbic acid, Flavor

PRINCIPAL DISPLAY PANEL

ORAL MAXIMUM STRENGTH PAIN RELIEF GEL

Benzocaine 20%

Anesthetic

NET WT 0.5 OZ (14 g)